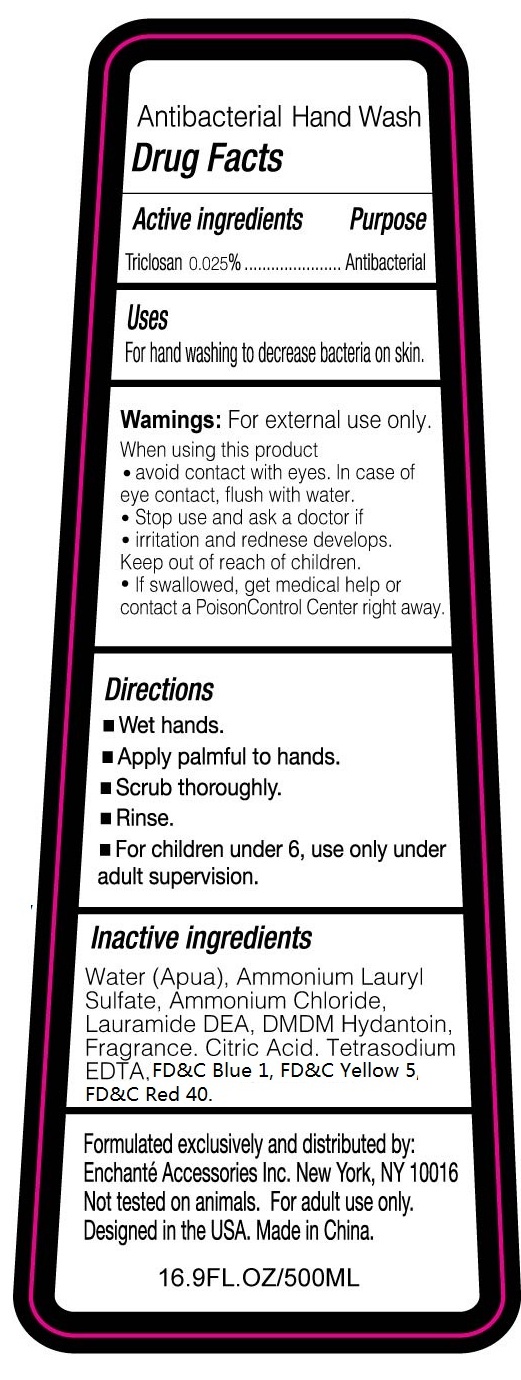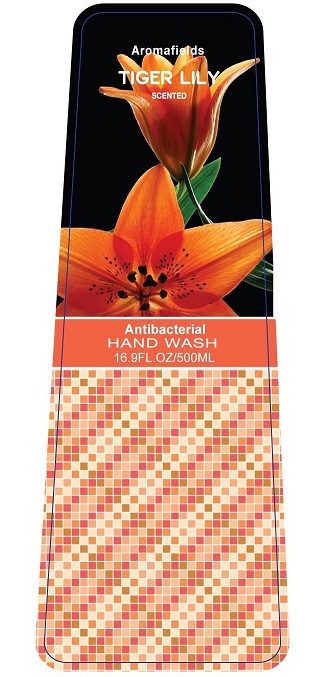 DRUG LABEL: Aromafields Tiger Lily Scented Antibacterial Hand Wash
NDC: 50563-401 | Form: LIQUID
Manufacturer: Enchante Accessories
Category: otc | Type: HUMAN OTC DRUG LABEL
Date: 20100709

ACTIVE INGREDIENTS: TRICLOSAN 0.025 mL/100 mL
INACTIVE INGREDIENTS: WATER; AMMONIUM LAURYL SULFATE; AMMONIUM CHLORIDE; LAURIC DIETHANOLAMIDE; DMDM HYDANTOIN; CITRIC ACID MONOHYDRATE; EDETATE SODIUM

AROMAFIELDS TIGER LILY SCENTED ANTIBACTERIAL HAND WASH

DRUG FACTS

Active Ingredients Purpose

Triclosan 0.025% ..........................Antibacterial

Uses

For handwashing to decrease bacteria on the skin

Warnings:

For external use only

When using this product

avoid contact with eyes. In case of eye contact, flush with water

Stop use and ask a doctor if irritation and redness develop

Keep out of reach of children.

If swallowed, get medical help or contact a poison control center right away

Directions

Wet hands
Apply palmful to hands
Scrub thoroughly
Rinse
For children under 6, use only under adult supervision

Inactive ingredients

Water (aqua), Ammonium Lauryl Sulfate, Ammonium chloride, Lauramide DEA, DMDM Hydantoin, fragrance, Citric Acid, Tertrasodium EDTA, FDandC Blue 1, FDandC Yello 5, FDandC Red 40.

Formulated exclusively and distributed by:
Enchante Accessories, Inc.
New York, NY 10016
Not Tested On Animals. For adult use only.
Designed in the USA
Made in China
16.9 fl.oz./500ml

PACKAGE LABEL

AROMAFIELDS
TIGER LILY
SCENTED
ANTIBACTERIAL
HAND WASH
16.9 fl. oz/500 ml